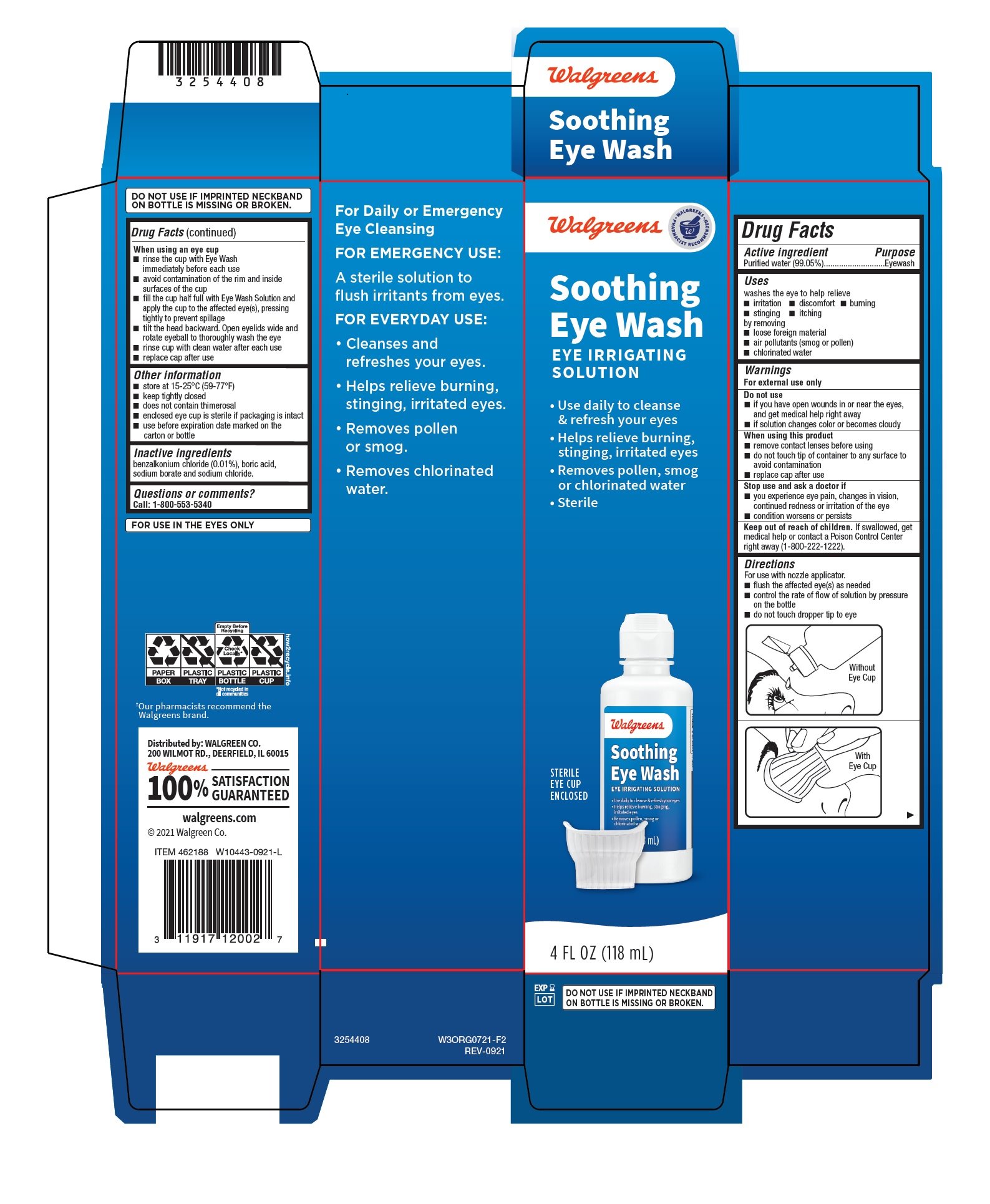 DRUG LABEL: Walgreens Sterile Soothing Eye Wash
NDC: 0363-0700 | Form: LIQUID
Manufacturer: Walgreens
Category: otc | Type: HUMAN OTC DRUG LABEL
Date: 20260114

ACTIVE INGREDIENTS: WATER 99.05 mL/100 mL
INACTIVE INGREDIENTS: BORIC ACID; SODIUM BORATE; SODIUM CHLORIDE; HYDROCHLORIC ACID; SODIUM HYDROXIDE; EDETATE DISODIUM; SORBIC ACID

Drug Facts

Active ingredient

Purified water (99.05%)

Purpose

Eyewash

Uses

washes the eye to help relieve

- irritation
- discomfort
- burning
- stinging by removing
- itching
- loose foreign material
- air pollutants (smog or pollen)
- chlorinated water

Warnings

For external use only

Do not use

- if you have open wounds in or near the eyes, and get medical help right away
- if solution changes color or becomes cloudy

When using this product

- remove contact lenses before using
- do not touch tip of container to any surface to avoid contamination
- replace cap after use

Stop use and ask a doctor if

- you experience eye pain, changes in vision, continued redness or irritation of the eye
- condition worsens or persists

Keep out of reach of children.

If swallowed, get medical help or contact a Poison Control Center right away (1-800-222-1222).

Directions

For use with a nozzle applicator.

- flush the affected eye(s) as needed
- control the rate of flow of solution by pressure on the bottle
- do not touch dropper tip to eye
- Without Eye Cup [image]
- With Eye Cup [image]

When using an eye cup

- rinse the cup with Eye Wash immediately before each use
- avoid contamination of the rim and inside surfaces of the cup
- fill the cup half full with Eye Wash Solution and apply the cup to the affected eye(s), pressing tightly to prevent spillage
- tilt the head backward. Open eyelids wide and rotate eyeball to thoroughly wash the eye
- rinse cup with clean water after each use
- replace cap after use

Other information

- store at 15°-25°C (59°-77°F)
- keep tightly closed
- does not contain thimerosal
- enclosed eye cup is sterile if packaging is intact
- use before expiration date marked on the carton or bottle

Inactive ingredients

benzalkonium chloride, (0.01%), boric acid, sodium borate and sodium chloride.

Questions or comments?

Call: 1-800-553-5340

FOR USE IN THE EYES ONLY

Distributed by: WALGREEN CO.
200 WILMOT RD., DEERFIELD, IL 60015

Walgreens
100% SATISFACTION GUARANTEED

walgreens.com

©2021 Walgreen Co.

3254408 W3ORG0721-F2

REV-0921

Package/Label Principal Display Panel

Walgreens

Soothing
Eye Wash

EYE IRRIGATING
SOLUTION

- Use daily to cleanse & refresh your eyes
- Helps relieve burning, stinging, irritated eyes
- Removes pollen, smog & chlorinated water
- Sterile

Sterile Eye Cup Enclosed

4 FL OZ (118 mL)

EXP
LOT
DO NOT USE IF IMPRINTED NECKBAND
ON BOTTLE IS MISSING OR BROKEN.